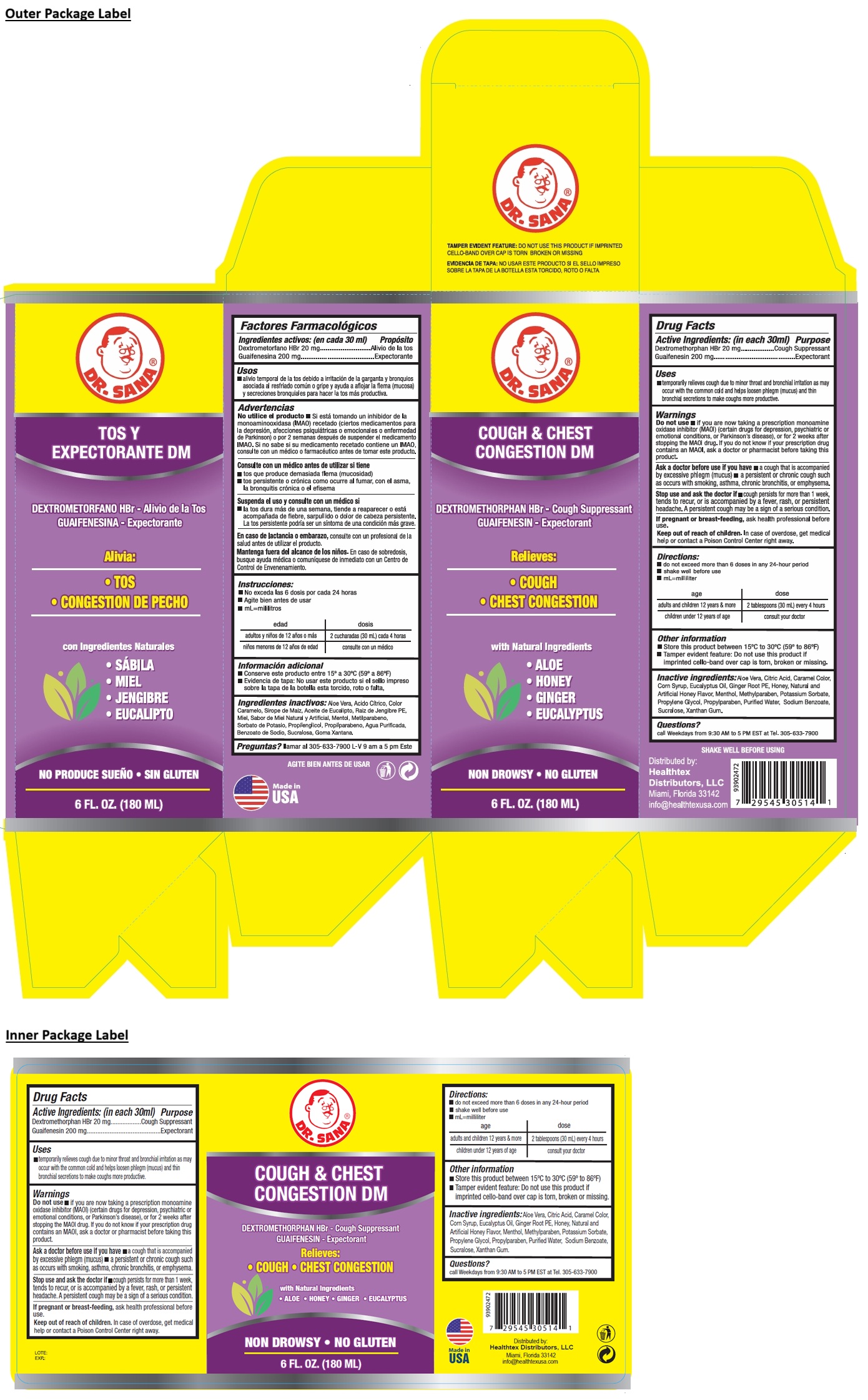 DRUG LABEL: DR. SANA COUGH AND CHEST CONGESTION DM
NDC: 53113-514 | Form: LIQUID
Manufacturer: GADAL Laboratories, Inc
Category: otc | Type: HUMAN OTC DRUG LABEL
Date: 20250722

ACTIVE INGREDIENTS: DEXTROMETHORPHAN HYDROBROMIDE 20 mg/30 mL; GUAIFENESIN 200 mg/30 mL
INACTIVE INGREDIENTS: ALOE VERA LEAF; CITRIC ACID MONOHYDRATE; CARAMEL; CORN SYRUP; EUCALYPTUS OIL; GINGER; HONEY; MENTHOL, UNSPECIFIED FORM; METHYLPARABEN; POTASSIUM SORBATE; PROPYLENE GLYCOL; PROPYLPARABEN; WATER; SODIUM BENZOATE; SUCRALOSE; XANTHAN GUM

DR. SANA® COUGH & CHEST CONGESTION DM

Active Ingredients: (in each 30ml)

Dextromethorphan HBr 20 mg
Guaifenesin 200 mg

Purpose

Cough Suppressant
Expectorant

Uses

• temporarily relieves cough due to minor throat and bronchial irritation as may occur with the common cold and helps loosen phlegm (mucus) and thin bronchial secretions to make coughs more productive.

Warnings

Do not use • if you are now taking a prescription monoamine oxidase inhibitor (MAOI) (certain drugs for depression, psychiatric or emotional conditions, or Parkinson's disease), or for 2 weeks after stopping the MAOI drug. If you do not know if your prescription drug contains an MAOI, ask a doctor or pharmacist before taking this product.

Ask a doctor before use if you have • a cough that is accompanied by excessive phlegm (mucus) • a persistent or chronic cough such as occurs with smoking, asthma, chronic bronchitis, or emphysema.

Stop use and ask the doctor if • cough persists for more than 1 week, tends to recur, or is accompanied by a fever, rash, or persistent headache. A persistent cough may be a sign of a serious condition.

If pregnant or breast-feeding, ask health professional before use.

Keep out of reach of children. In case of overdose, get medical help or contact a Poison Control Center right away.

Directions:

do not exceed more than 6 doses in any 24-hour period
shake well before use
mL=milliliter

age | dose
adults and children 12 years & more | 2 tablespoons (30 mL) every 4 hours
children under 12 years of age | consult your doctor

Other information

• Store this product between 15°C to 30°C (59° to 86°F)
• Tamper evident feature: Do not use this product if imprinted cello-band over cap is torn, broken or missing.

Inactive ingredients:

Aloe Vera, Citric Acid, Caramel Color, Corn Syrup, Eucalyptus Oil, Ginger Root PE, Honey, Natural and Artificial Honey Flavor, Menthol, Methylparaben, Potassium Sorbate, Propylene Glycol, Propylparaben, Purified Water, Sodium Benzoate, Sucralose, Xanthan Gum.

Questions?

call Weekdays from 9:30 AM to 5 PM EST at Tel. 305-633-7900

Relieves:
• COUGH
• CHEST CONGESTION

with Natural Ingredients
• ALOE
• HONEY
• GINGER
• EUCALYPTUS

NON DROWSY • NO GLUTEN

Distributed by:
Healthtex Distributors, LLC
Miami, Florida 33142
info@healthtexusa.com

Made in USA

TAMPER EVIDENT FEATURE: DO NOT USE THIS PRODUCT IF IMPRINTED CELLO-BAND OVER CAP IS TORN BROKEN OR MISSING